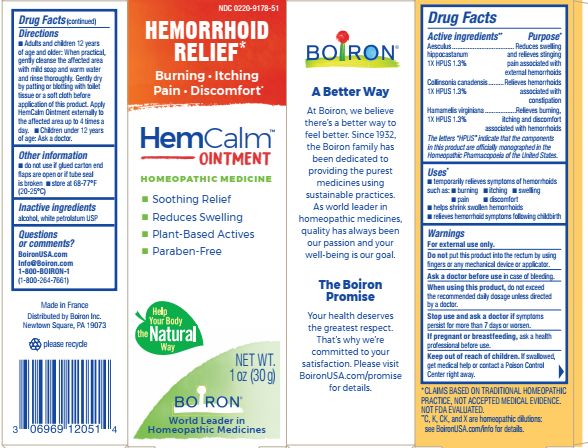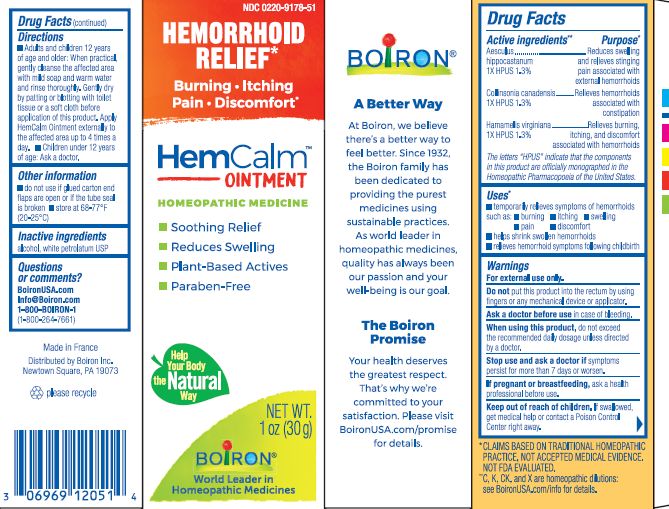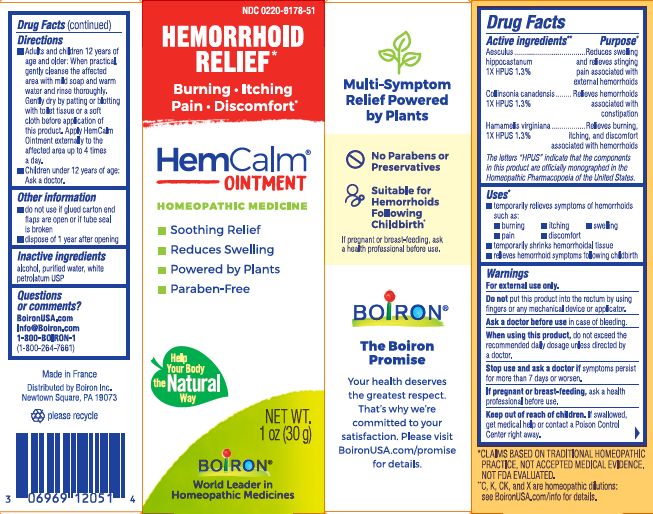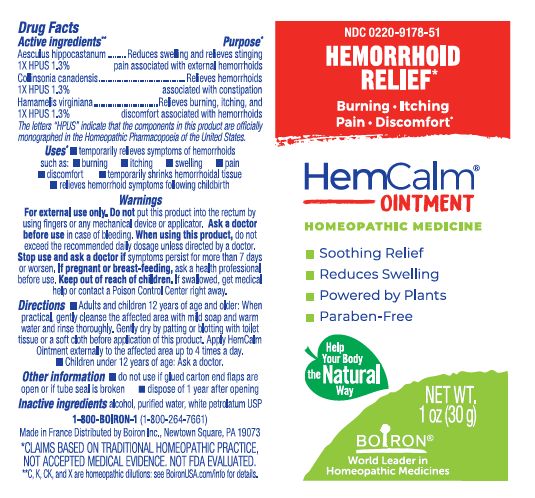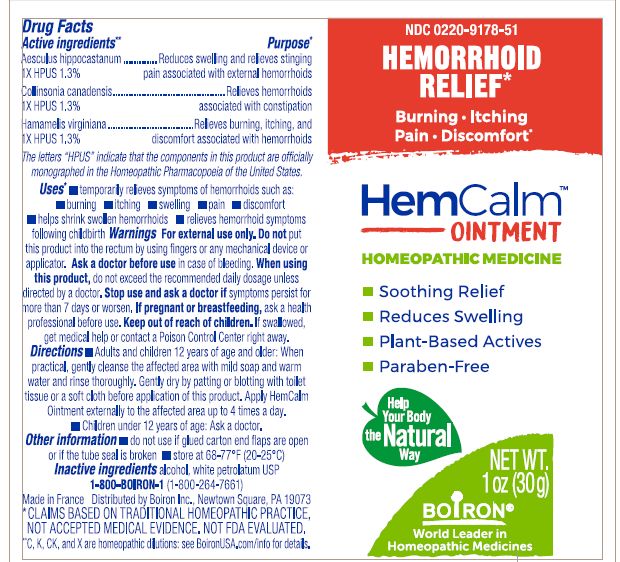 DRUG LABEL: HemCalm
NDC: 0220-9178 | Form: OINTMENT
Manufacturer: BOIRON
Category: homeopathic | Type: HUMAN OTC DRUG LABEL
Date: 20240216

ACTIVE INGREDIENTS: HAMAMELIS VIRGINIANA ROOT BARK/STEM BARK 1 [hp_X]/1 1; COLLINSONIA CANADENSIS ROOT 1 [hp_X]/1 1; HORSE CHESTNUT 1 [hp_X]/1 1
INACTIVE INGREDIENTS: PETROLATUM; ALCOHOL; WATER

HEMCALM OINTMENT

Active ingredients**

Aesculus hippocastanum 1X HPUS 1.3%

Collinsonia canadensis 1X HPUS 1.3%

Hamamelis virginiana 1X HPUS 1.3%

The letters "HPUS" indicate that the components in this product are officially monographed in the Homeopathic Pharmacopoeia of the United States.

Purpose*

Aesculus hippocastanum 1X HPUS 1.3% ... Reduces swelling and relieves stinging pain associated with external hemorrhoids

Collinsonia canadensis 1X HPUS 1.3% ... Relieves hemorrhoids associated with constipation

Hamamelis virginiana 1X HPUS 1.3% … Relieves burning, itching, and discomfort associated with hemorrhoids

Uses*

▪ temporarily relieves symptoms of hemorrhoids such as: ▪ burning ▪ itching ▪ swelling ▪ pain

▪ discomfort

▪ helps shrink swollen hemorrhoids

▪ relieves hemorrhoid symptoms following childbirth

WARNINGS

For external use only.

DO NOT USE

Do not put this product into the rectum by using fingers or any mechanical device or applicator.

Ask a doctor before use in case of bleeding.

Stop use and ask a doctor if symptoms persist for more than 7 days or worsen.

PREGNANCY OR BREAST FEEDING

If pregnant or breast-feeding, ask a health professional before use.

Keep out of reach of children. If swallowed, get medical help or contact a Poison Control Center right away.

DOSAGE AND ADMINISTRATION

- Adults and children 12 years of age and older: When practical, gently cleanse the affected area with mild soap and warm water and rinse thoroughly. Gently dry by patting or blotting with toilet tissue or a soft cloth before application of this product. Apply HemCalm Ointment externally to the affected area up to 4 times a day.
- Children under 12 years of age: Ask a doctor.

do not use if glued carton end flaps are open or if tube seal is broken

dispose of 1 year after opening

1 oz (30 g)

Hemorrhoid Relief*

Burning Itching Pain Discomfort

*CLAIMS BASED ON TRADITIONAL HOMEOPATHIC PRACTICE NOT ACCEPTED MEDICAL EVIDENCE. NOT FDA EVALUATED.
*C,K,CK, and X are homeopathic dilutions: see BoironUSA.com/info for details.

INACTIVE INGREDIENT

alcohol, purified water, white petrolatum USP

QUESTIONS

BoironUSA.com Info@boiron.com

1-800-BOIRON-1
(1-800-264-7661)

Distributed by Boiron, Inc.

Newtown Square, PA 19073